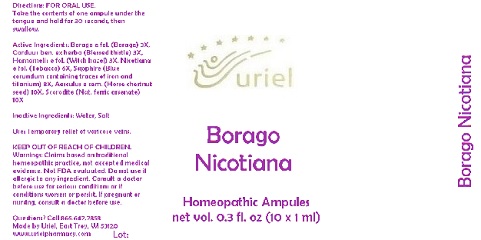 DRUG LABEL: Borago Nicotiana
NDC: 48951-2077 | Form: LIQUID
Manufacturer: Uriel Pharmacy Inc.
Category: homeopathic | Type: HUMAN OTC DRUG LABEL
Date: 20180518

ACTIVE INGREDIENTS: BORAGE 3 [hp_X]/1 mL; CENTAUREA BENEDICTA 3 [hp_X]/1 mL; HAMAMELIS VIRGINIANA LEAF 3 [hp_X]/1 mL; TOBACCO LEAF 6 [hp_X]/1 mL; ALUMINUM OXIDE 8 [hp_X]/1 mL; HORSE CHESTNUT 10 [hp_X]/1 mL; FERROUS ARSENATE 10 [hp_X]/1 mL
INACTIVE INGREDIENTS: WATER; SODIUM CHLORIDE

Borago Nicotiana

INDICATIONS AND USAGE

Directions: FOR ORAL USE.

DOSAGE AND ADMINISTRATION

Take the contents of one ampule under the tongue and hold for 30 seconds, then swallow.

ACTIVE INGREDIENT

Active Ingredients: Borago e fol. 3X, Carduus ben. ex herba 3X, Hamamelis e fol. 3X, Nicotiana e fol. 6X, Sapphire 8X, Aesculus e sem. 10X, Scorodite 10X

Inactive Ingredients: Water, Salt

PURPOSE

Use: Temporary relief of varicose veins.

KEEP OUT OF REACH OF CHILDREN.

WARNINGS

Warnings: Claims based on traditional homeopathic practice, not accepted medical evidence. Not FDA evaluated. Do not use if allergic to any ingredient. Consult a doctor before use for serious conditions or if conditions worsen or persist. If pregnant or nursing, consult a doctor before use.

QUESTIONS

Questions? Call 866.642.2858 Made by Uriel, East Troy, WI 53120 www.urielpharmacy.com